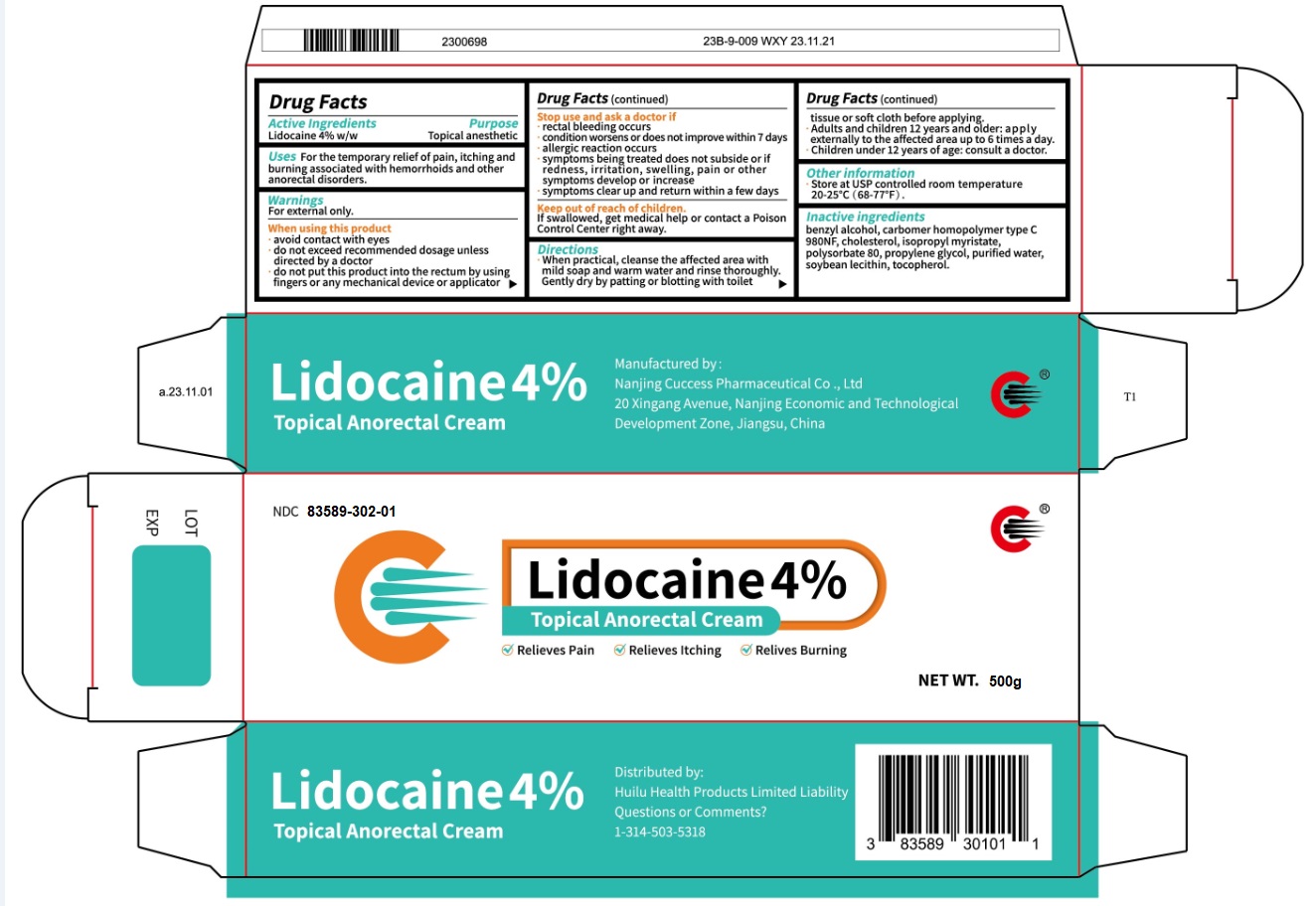 DRUG LABEL: Lidocaine
NDC: 83589-302 | Form: CREAM
Manufacturer: Nanjing Chengong Pharmaceutical Co., Ltd.
Category: otc | Type: HUMAN OTC DRUG LABEL
Date: 20260105

ACTIVE INGREDIENTS: LIDOCAINE 20 g/500 g
INACTIVE INGREDIENTS: BENZYL ALCOHOL; PROPYLENE GLYCOL; TOCOPHEROL; ISOPROPYL MYRISTATE; POLYSORBATE 80; SOYBEAN LECITHIN; CARBOMER HOMOPOLYMER TYPE C; CHOLESTEROL

Active Ingredients

Lidocaine 4% w/w

Purpose

Topical anesthetic

Uses

For the temporary relief of pain, itching and burning associated with hemorrhoids and other anorectal disorders.

Warnings

For external only.

When using this product

- avoid contact with eyes
- do not exceed recommended dosage unless directed by a doctor
- do not put this product into the rectum by using fingers or any mechanical device or applicator

Stop use and ask a doctor if

- rectal bleeding occurs
- condition worsens or does not improve within 7 days
- allergic reaction occurs
- symptoms being treated does not subside or if redness, irritation, swelling, pain or other symptoms develop or increase
- symptoms clear up and return within a few days

Keep out of reach of children.

If swallowed, get medical help or contact a Poison Control Center right away.

Directions

- When practical, cleanse the affected area with mild soap and warm water and rinse thoroughly.Gently dry by patting or blotting with toilet tissue or soft cloth before applying.
- Adults and children 12 years and older: apply eyternally to the attected area un to 6 times a day.
- Children under 12 years of age: consult a doctor.

Other information

Store at USP controlled room temperature 20-25℃ (68-77°F).

Inactive ingredient

benzyl alcohol, carbomer homopolymer type C 980NF, cholesterol, isopropyl myristate, polysorbate 80, propylene glycol, purified water, soybean lecithin, tocopherol.